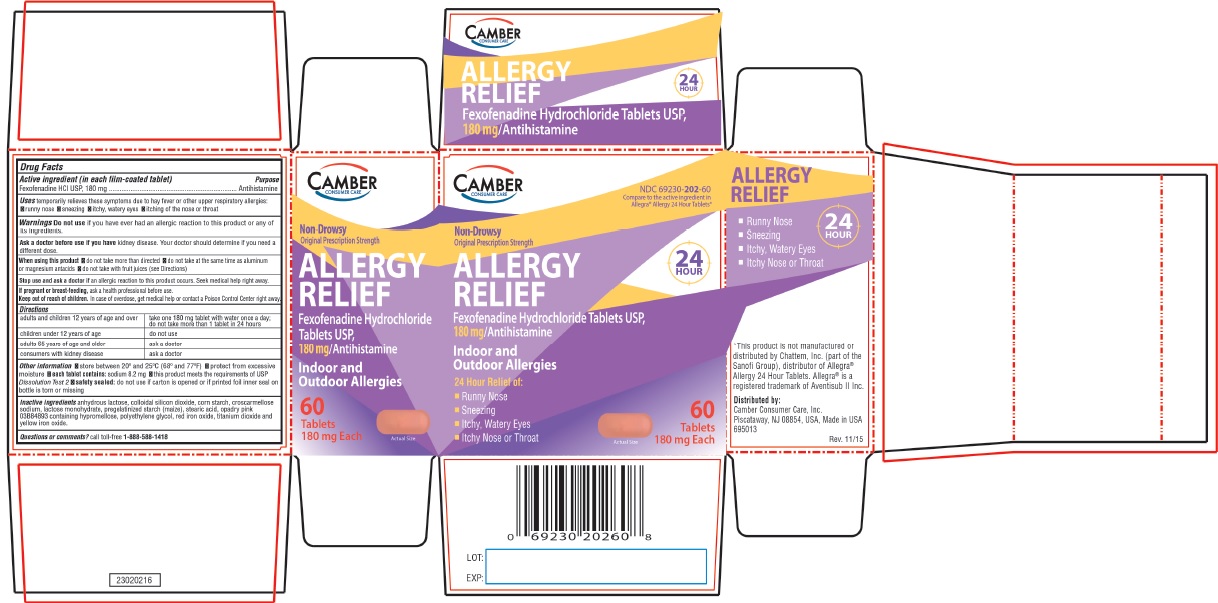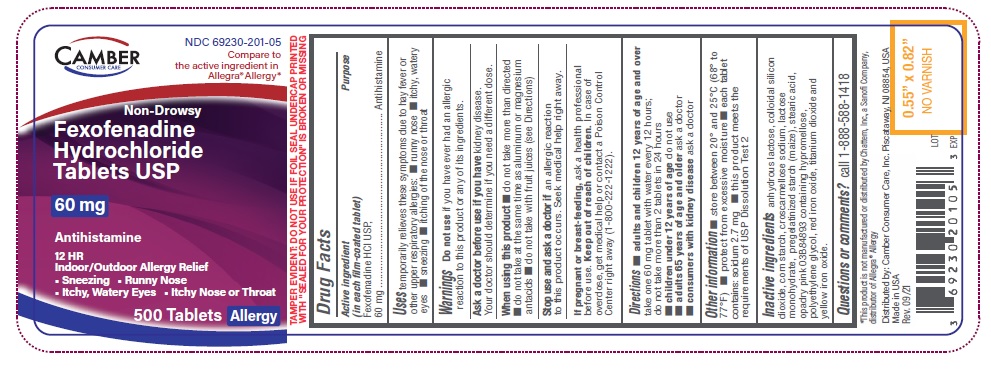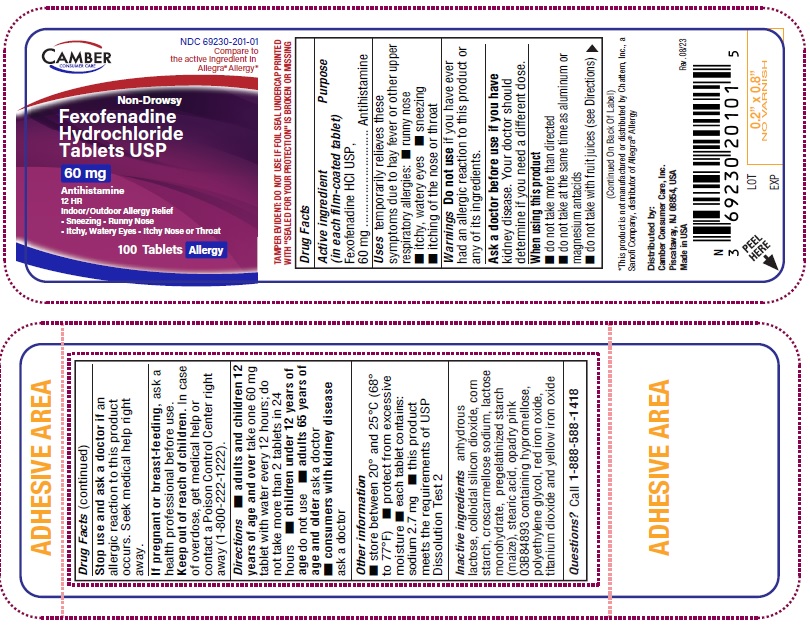 DRUG LABEL: Fexofenadine HCl
NDC: 69230-202 | Form: TABLET, FILM COATED
Manufacturer: Camber Consumer Care
Category: otc | Type: HUMAN OTC DRUG LABEL
Date: 20231106

ACTIVE INGREDIENTS: FEXOFENADINE HYDROCHLORIDE 180 mg/1 1
INACTIVE INGREDIENTS: ANHYDROUS LACTOSE; SILICON DIOXIDE; STARCH, CORN; CROSCARMELLOSE SODIUM; LACTOSE MONOHYDRATE; STEARIC ACID; HYPROMELLOSE, UNSPECIFIED; POLYETHYLENE GLYCOL, UNSPECIFIED; FERRIC OXIDE RED; TITANIUM DIOXIDE; FERRIC OXIDE YELLOW

FEXOFENADINE HYDROCHLORIDE TABLETS USP, 60mg and 180 mg
Allergy

ALLERGY Active ingredient (in each film-coated tablet)

Fexofenadine HCl USP, 60mg and 180 mg

Purpose

Antihistamine

Uses

temporarily relieves these symptoms due to hay fever or other upper respiratory allergies:

- runny nose
- itchy, watery eyes
- sneezing
- itching of the nose or throat

Warnings

Do not use

if you have ever had an allergic reaction to this product or any of its ingredients.

Ask a doctor before use if you have

kidney disease. Your doctor should determine if you need a different dose.

When using this product

- do not take more than directed
- do not take at the same time as aluminum or magnesium antacids
- do not take with fruit juices (see Directions)

Stop use and ask a doctor if

an allergic reaction to this product occurs. Seek medical help right away.

If pregnant or breast-feeding,

ask a health professional before use.

Keep out of reach of children.

In case of overdose, get medical help or contact a Poison Control Center right away (1800-222-1222).

Directions

FOR 60mg
adults and children 12 years of age and over | take two 60mg tablets with water evrery 12 hours; do not take more than 2 tablets in 24 hours
children under 12 years of age | do not use
adults 65 years of age and older | ask a doctor
consumers with kidney disease | ask a doctor

FOR 180mg
adults and children 12 years of age and over | take one 180mg tablet with water once a day; do not take more than 1 tablet in 24 hours
children under 12 years of age | do not use
adults 65 years of age and older | ask a doctor
consumers with kidney disease | ask a doctor

Other information

- safety sealed: do not use if carton is opened or if printed foil inner seal on bottle is torn or missing
- store between 20° and 25°C (68° and 77°F)
- protect from excessive moisture
- each tablet contains: sodium 8.2 mg (for 180mg)
- each tablet contains: sodium 2.7 mg (for 60mg)
- this product meets the requirements of USP Dissolution Test 2

Inactive ingredients

anhydrous lactose, colloidal silicon dioxide, corn starch, croscarmellose sodium, lactose monohydrate, pregelatinized starch (maize), stearic acid, opadry pink 03B84893 containing hypromellose, polyethylene glycol, red iron oxide, titanium dioxide and yellow iron oxide.

Questions or comments?

Call 1-888-588-1418

Distributed by:
Camber Consumer Care, Inc.
Piscataway, NJ 08854, USA,

Made in USA

CAMBER CONSUMER CARE

NDC 69230-201-01 Compare to the active ingredient in Allegra® Allergy*

Non-Drowsy

Fexofenadine Hydrochloride Tablets USP

60 mg

Antihistamine

12 HR Indoor/Outdoor Allergy Relief

Sneezing
Runny Nose
Itchy, Watery Eyes
Itchy Nose or Throat

NDC 69230-201-05 Compare to the active ingredient in Allegra® Allergy*

Non-Drowsy

Fexofenadine Hydrochloride Tablets USP

60 mg

Antihistamine

12 HR Indoor/Outdoor Allergy Relief

- Sneezing
- Runny Nose
- Itchy, Watery Eyes
- Itchy Nose or Throat